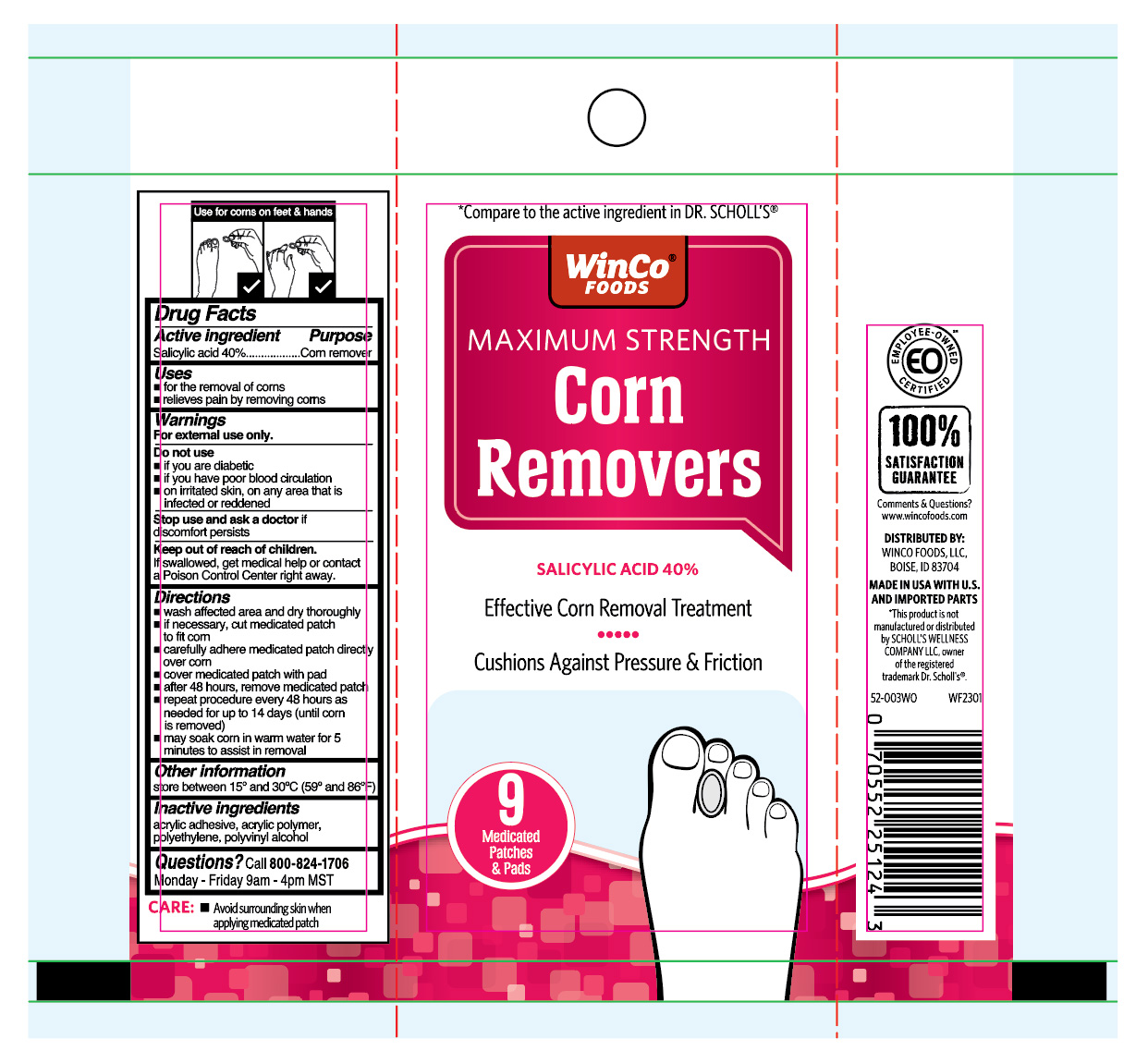 DRUG LABEL: Corn Removers
NDC: 67091-750 | Form: PATCH
Manufacturer: WinCo Foods LLC
Category: otc | Type: HUMAN OTC DRUG LABEL
Date: 20260102

ACTIVE INGREDIENTS: SALICYLIC ACID 400 mg/1 g
INACTIVE INGREDIENTS: POLYVINYL ALCOHOL, UNSPECIFIED; HIGH DENSITY POLYETHYLENE

WinCo Maximum Strength Corn Removers

Active ingredient

Salicylic acid 40%

Purpose

Corn remover

Uses

- for the removal of corns
- relieves pain by removing corns

Warnings

For external use only.

Do not use

- if you are diabetic
- if you have poor blood circulation
- on irritated skin, on any area that is infected or reddened

Stop use and ask a doctor if

discomfort persists

Keep out of reach of children.

If swallowed, get medical help or contact a Poison Control Center right away.

Directions

- wash affected area and dry thoroughly
- if necessary, cut medicated patch to fit corn
- carefully adhere medicated patch directly over corn
- cover medicated patch with pad
- after 48 hours, remove medicated patch
- repeat procedure every 48 hours as needed for up to 14 days (until corn is removed)
- may soak corn in warm water for 5 minutes to assist in removal

Other information

store between 15° and 30°C (59° and 86°F)

Inactive ingredients

acrylic adhesive, acrylic polymer, polyethylene, polyvinyl alcohol

Questions?

call 800-824-1706

Monday - Friday 9am - 4pm MST

Principal Display Panel

WinCo FOODS

MAXIMUM STRENGTH

Corn

Removers

Salicylic Acid 40%

- Effective Corn Removal Treatment
- Cushions Against Pressure & Fiction

9 Medicated Patches & Pads